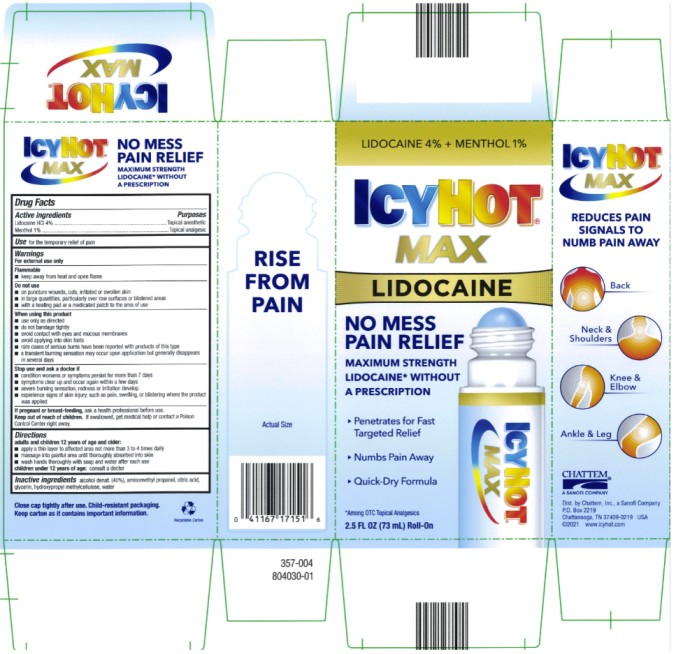 DRUG LABEL: Icy Hot with Lidocaine No-Mess
NDC: 41167-1715 | Form: LIQUID
Manufacturer: Chattem, Inc.
Category: otc | Type: HUMAN OTC DRUG LABEL
Date: 20260114

ACTIVE INGREDIENTS: LIDOCAINE 4 g/100 g; MENTHOL 1 g/100 g
INACTIVE INGREDIENTS: ALCOHOL; AMINOMETHYLPROPANOL; CITRIC ACID MONOHYDRATE; GLYCERIN; HYPROMELLOSE, UNSPECIFIED; WATER

Icy Hot with Lidocaine No-Mess Applicator

ICY HOT with LIDOCAINE NO MESS

Drug Facts

Purposes

Lidocaine HCl 4%............................................................................................................................Topical anesthetic

Menthol 1%.......................................................................................................................................Topical analgesic

Warnings

For external use only

Flammable

■ keep away from heat and open flame

Do not use

■ on puncture wounds, cuts, irritated or swollen skin

■ in large quantities, particularly over raw surfaces or blistered areas

■ with a heating pad or a medicated patch to the area of use

When using this product

■ use only as directed

■ do not bandage tightly

■ avoid contact with eyes and mucous membranes

■ avoid applying into skin folds

■ rare cases of serious burns have been reported with products of this type

■ a transient burning sensation may occur upon application but generally disappears in several days

Stop use and ask a doctor if

■ condition worsens or symptoms persist for more than 7 days

■ symptoms clear up and occur again within a few days

■ severe burning sensation, redness or irritation develop

■ experience signs of skin injury, such as pain, swelling, or blistering where the product was applied

If pregnant or breast-feeding,

ask a health professional before use.

Keep out of reach of children.

If swallowed, get medical help or contact a Poison Control Center right away.

Directions

adults and children 12 years of age and older:

■ apply a thin layer to affected area not more than 3 to 4 times daily

■ massage into painful area until thoroughly absorbed into skin

■ wash hands thoroughly with soap and water after each use

children under 12 years of age: consult a doctor

Inactive ingredients:

alcohol denat. (40%), aminomethyl propanol, citric acid, glycerin, hydroxypropyl methylcellulose, water

PRINCIPAL DISPLAY PANEL

ICY HOT
LIDOCAINE
Plus Menthol
NO MESS

Applicator
NET WT 2.5 oz (70.8 g)